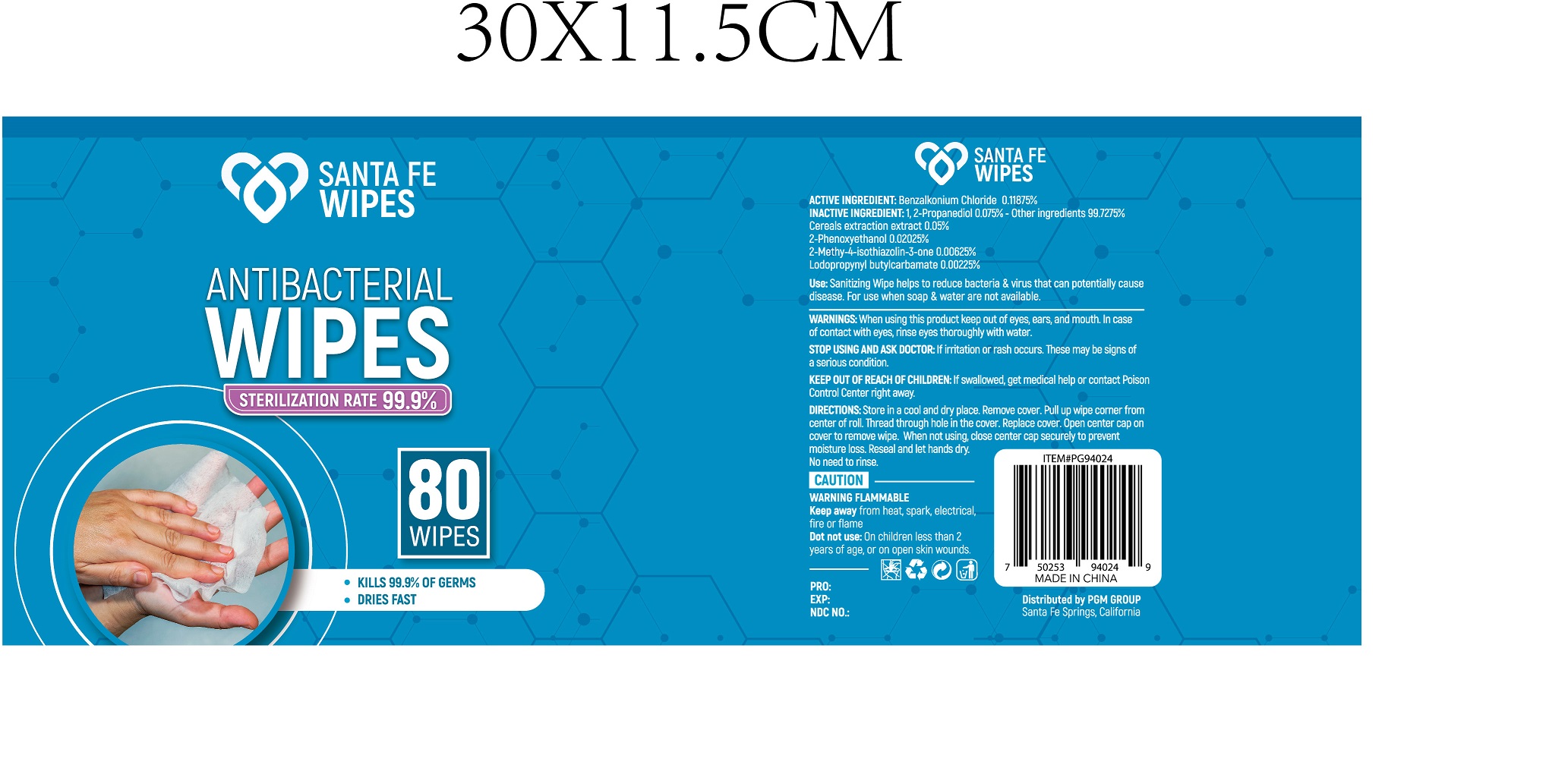 DRUG LABEL: Antibacterial wipes
NDC: 78356-216 | Form: CLOTH
Manufacturer: Zhejiang Yiwu Anrou Sanitation Article Co., Ltd
Category: otc | Type: HUMAN OTC DRUG LABEL
Date: 20200906

ACTIVE INGREDIENTS: BENZALKONIUM CHLORIDE 5 mg/1 1
INACTIVE INGREDIENTS: PROPYLENE GLYCOL; WATER; IODOPROPYNYL BUTYLCARBAMATE 0.0945 mg/1 1; METHYLISOTHIAZOLINONE 0.2625 mg/1 1; BARLEY 2.1 mg/1 1; PHENOXYETHANOL 0.84 mg/1 1

Anrou-PGM, Antibacterial wipes, Benzalkonium Chloride (rev)

ACTIVE INGREDIENT

Benzalkonium Chloride, 0.11875% w/v ...... Purpose: Antibacterial

Purpose

Antibacterial

WARNINGS

When using this product keep out of eyes, ears, and mouth. In case of contact with eyes, rinse eyes throughly with water.

Do not use

On children less than 2 years of age, or on open skin wounds.

STOP USING AND ASK DOCTOR

If irritation or rash occurs. These may be signs of a serious condition.

KEEP OUT OF REACH OF CHILDREN

If swallowed, get medical help or contact Poison Control Center right away.

Use

Sanitizing Wipe helps to reduce bacteria & virus that can potentially cause disease.

For use when soap & water are not available.

DIRECTIONS

Store in a cool and dry place.

Romove cover.

Pull up wipe corner from center of roll.

Thread through hole in the cover.

Replace cover.

Open center cap on cover to remove wipe.

When not using, close center cap securely to prevent moisture loss.

Reseal and let hands dry.

No need to rinse.

CAUTION

WARNING FLAMMABLE

Keep away from heat, spark, electrical, fire or flame.

STORAGE AND HANDLING

Store in a cool and dry place.

INACTIVE INGREDIENT

1,2-Propanediol, Cereals Extraction Extract, 2-Phenoxyethanol, 2-Methy-4-isothiazolin-3-one, Iodopropynyl Butylcarbamate, Water